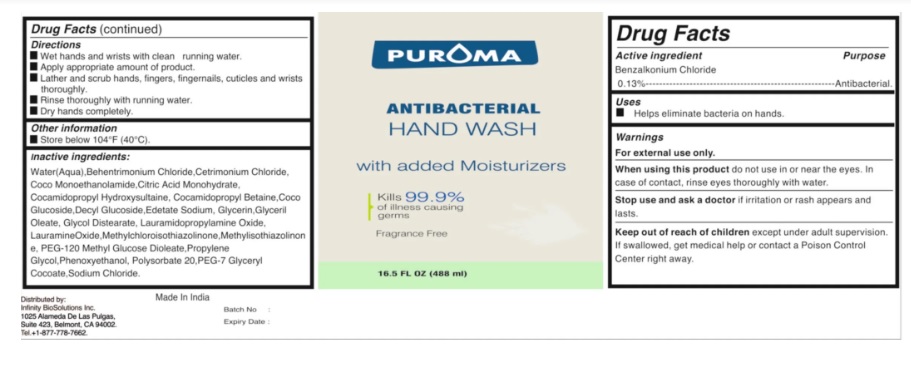 DRUG LABEL: PUROMA  Antibacterial Hand Wash Fragrance Free
NDC: 80948-006 | Form: LIQUID
Manufacturer: ZENITH MICRO CONTROL
Category: otc | Type: HUMAN OTC DRUG LABEL
Date: 20231214

ACTIVE INGREDIENTS: BENZALKONIUM CHLORIDE 130 mg/100 mL
INACTIVE INGREDIENTS: WATER; METHYLCHLOROISOTHIAZOLINONE; GLYCERIN; METHYLISOTHIAZOLINONE; CETRIMONIUM CHLORIDE; LAURAMIDOPROPYLAMINE OXIDE; COCO MONOETHANOLAMIDE; PROPYLENE GLYCOL; CITRIC ACID MONOHYDRATE; PHENOXYETHANOL; EDETATE SODIUM; SODIUM CHLORIDE; DECYL GLUCOSIDE; COCO GLUCOSIDE; GLYCERYL OLEATE; COCAMIDOPROPYL BETAINE; LAURAMINE OXIDE; BEHENTRIMONIUM CHLORIDE; PEG-7 GLYCERYL COCOATE; COCAMIDOPROPYL HYDROXYSULTAINE; GLYCOL DISTEARATE; POLYSORBATE 20; PEG-120 METHYL GLUCOSE DIOLEATE

Active ingredient

Benzalkonium chloride 0.13%

Purpose

Antibacterial

Uses

Hand Sanitizer to help reduce bacteria on skin.

Warnings

For external use only.
When using this product do not use in or near the eyes. In case of contact, rinse eyes thoroughly with water.
Stop use and ask a doctor if irritation or rash appears and lasts.

Keep out of reach of children

except under adult supervision. If swallowed, get medical help or contact a Poison Control Center right away.

Directions

• Wet hands and wrists with clean running water
• Apply appropriate amount of product
• Lather and scrub hands, fingers, fingernails, cuticles and wrists thoroughly
• Rinse thoroughly with running water
• Dry hands completely.

Inactive ingredients

Water, Glycerin, Methylchloroisothiazolinone, Methylisothiazolinone, Cetrimonium Chloride, Lauramidopropylamine Oxide , Coco Monoethanolamide, PEG-120 Methyl Glucose Dioleate, Propylene Glycol, Citric Acid Monohydrate, Phenoxyethanol, Edetate Sodium , Sodium Chloride, Decyl Glucoside, Coco Glucoside, Glyceril Oleate, Cocamidopropyl Betaine, Lauramine Oxide, Behentrimonium Chloride PEG-7 Glyceryl Cocoate, Cocamidopropyl Hydroxysultaine, Glycol Distearate, Polysorbate 20.

Other information

• Store below 104°F (40°C)